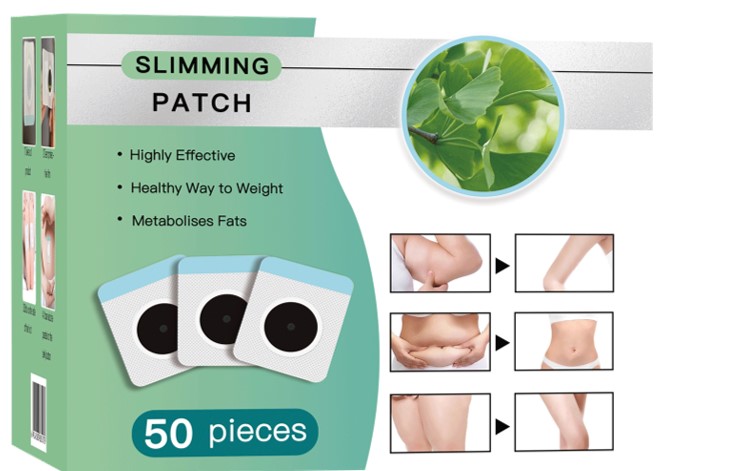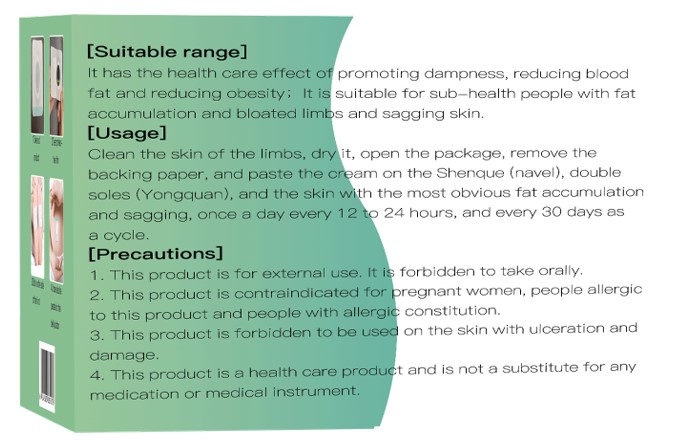 DRUG LABEL: Magnet molding honey pastes
NDC: 52784-020 | Form: PATCH
Manufacturer: ZHENGZHOU GIANT BIOCHEMISTRY GROUP CO.,LTD
Category: homeopathic | Type: HUMAN OTC DRUG LABEL
Date: 20231204

ACTIVE INGREDIENTS: GINGER OIL 10 g/100 g
INACTIVE INGREDIENTS: GINKGO; ZANTHOXYLUM BUNGEANUM WHOLE; ALISMA PLANTAGO-AQUATICA SUBSP. ORIENTALE ROOT; EUCALYPTUS OIL; CINNAMON OIL; SENNA LEAF; SYNTHETIC BEESWAX; HONEY; SAFFLOWER; CLOVE; FU LING; FERROSOFERRIC OXIDE; PERILLA FRUTESCENS LEAF

Magnet molding honey paste

ACTIVE INGREDIENT

GINGER OIL

PURPOSE

It has the health care effect ofpromoting dampness, reducing bloodfat and reducing obesity ; It issuitable for sub-health people with fataccumulation and bloated limbs and sagging skin.

Keep out of reach of children

INDICATIONS AND USAGE

Clean the skin of the limbs, dry it, open the package, remove thebacking paper, and paste the cream on the Shenque (navel), doublesoles (Yongquan), and the skin with the most obvious fat accumulationand sagging, once a day every 12 to 24 hours, and every 30 days asa cycle.

WARNINGS

1. This product is for external use. It is forbidden to take orally.
2. This product is contraindicated for pregnant women, people allergic
to this product and people with allergic constitution.
3.This product is forbidden to be used on the skin with ulceration and damage.
4. This product is a health care product and is not a substitute for any medication or medical instrument.

DOSAGE AND ADMINISTRATION

Clean the skin of the limbs, dry it, open the package, remove thebacking paper, and paste the cream on the Shenque (navel), doublesoles (Yongquan), and the skin with the most obvious fat accumulationand sagging, once a day every 12 to 24 hours, and every 30 days asa cycle.

STORAGE AND HANDLING

Store in a cool and dry place

INACTIVE INGREDIENT

GINKGO
ZANTHOXYLUM BUNGEANUM WHOLE
ALISMA PLANTAGO-AQUATICA SUBSP. ORIENTALE ROOT
EUCALYPTUS OIL
CINNAMON OIL
SENNA LEAF
SYNTHETIC BEESWAX
HONEY
SAFFLOWER
CLOVE
FU LING
FERROSOFERRIC OXIDE
PERILLA FRUTESCENS LEAF